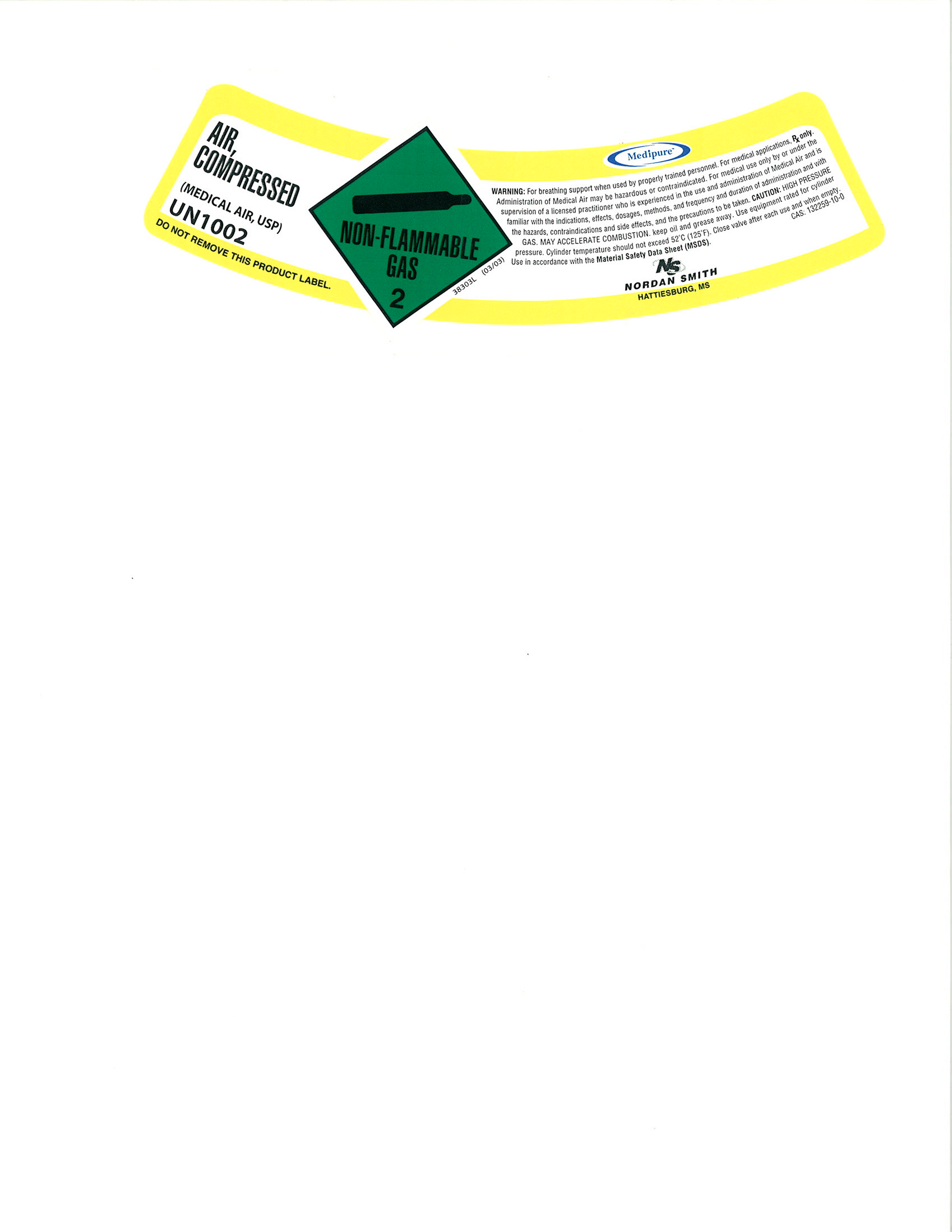 DRUG LABEL: Air
NDC: 54416-004 | Form: GAS
Manufacturer: Nordan Smith Welding Supply
Category: prescription | Type: HUMAN PRESCRIPTION DRUG LABEL
Date: 20100813

ACTIVE INGREDIENTS: Air 215 mL/1 L

Air

PACKAGE LABEL

AIR, COMPRESSED
(MEDICAL AIR, USP)
UN1002
DO NOT REMOVE THIS PRODUCT LABEL.
NON-FLAMMBLE GAS 2
Medipure
WARNING: For breathing support when used by properly trained personnel. For medical applications. RX only. Administration of Medical Air may be hazardous or contraindicated. For medical use only by or under the supervision of a licensed practitioner who is experienced in the use and administration of Medical Air and is familiar with the indications, effects, dosages, methods, and frequency and duration of administration and with the hazards, contraindications and side effects, and the precautions to be taken. CAUTION: HIGH PRESSURE GAS. MAY ACCELERATE COMBUSTION. Keep oil and grease away. Use equipment rated for cylinder pressure. Cylinder temperature should not exceed 52°C (125°F). Close Valve after each use and when empty. Use in accordance with the Material Safety Data Sheet (MSDS). CAS: 132259-10-0
N/S NORDAN SMITH HATTIESBURG, MS. 38303L (03/03)